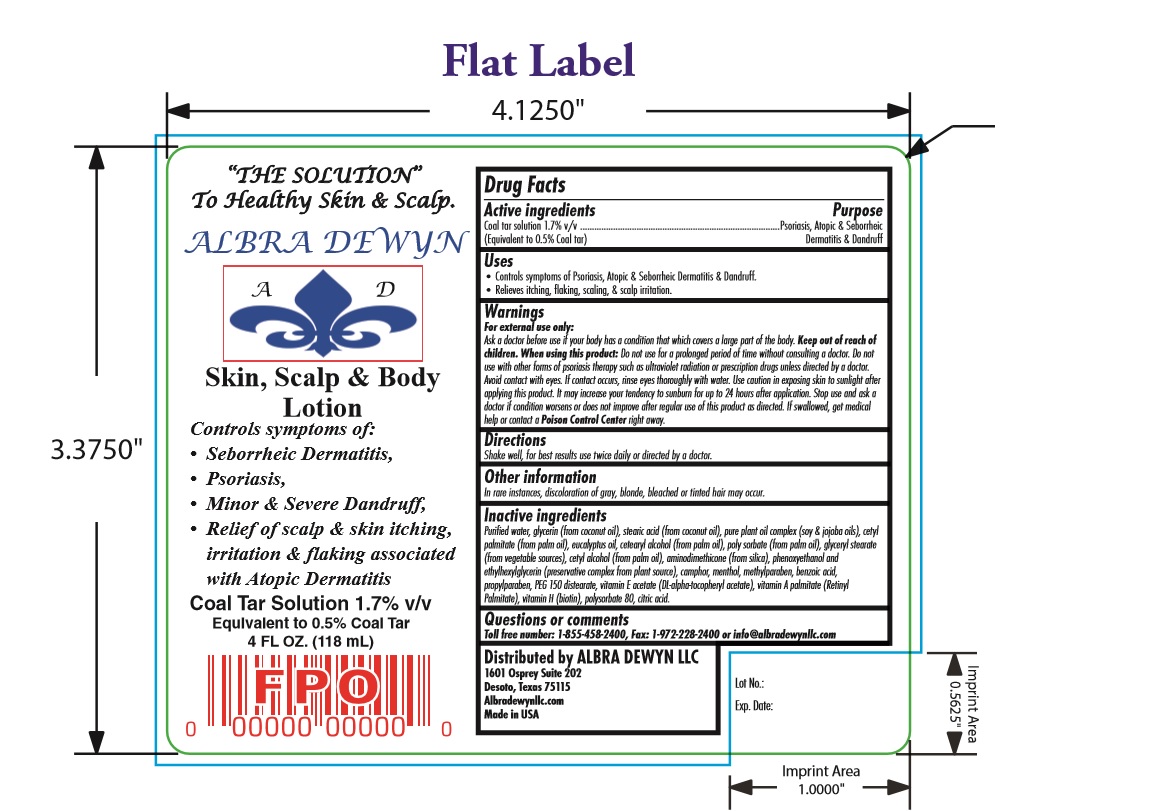 DRUG LABEL: Skin and Scalp Body
NDC: 59151-646 | Form: LOTION
Manufacturer: Albra Dewyn LLC
Category: otc | Type: HUMAN OTC DRUG LABEL
Date: 20161011

ACTIVE INGREDIENTS: COAL TAR 0.5 mg/1 mL
INACTIVE INGREDIENTS: CAMPHOR (SYNTHETIC); PEG-150 DISTEARATE; BIOTIN; CITRIC ACID MONOHYDRATE; WATER; ETHYLHEXYLGLYCERIN; PROPYLPARABEN; PHENOXYETHANOL; MENTHOL; METHYLPARABEN; BENZOIC ACID; .ALPHA.-TOCOPHEROL ACETATE, D-; VITAMIN A PALMITATE; GLYCERIN; SOYBEAN OIL; CETYL PALMITATE; EUCALYPTUS OIL; CETYL ALCOHOL; AMODIMETHICONE (800 CST); STEARIC ACID; JOJOBA OIL; POLYSORBATE 80; GLYCERYL MONOSTEARATE

Skin & Scalp Lotion

Uses

Controls symptoms of psoriasis, Atopic & Seborrheic Dermatitis & Dandruff.

Relieves itching, flaking, scaling & scalp irritation.

Warnings

For external use only:

Ask a doctor before use if your body has a condition that which convers a large part of the body. Keep out of reach of children. when using this product: do not use for a prolonged period of time without consulting a doctor. Do not use with other forms of psoriasis therapy such as ultrviolet radiation or prescription drugs unless directed by a doctor. Avoid contact with eyes. if contact occurs, rinse eys thoroughly with water. Use cation in exposing skin to sunlght after applying this product. It may increase your tendecy to sunburn for up to 24 hours after application. Stop use and ask a doctor if condition worsens or does not improve after regular use of this product as directed. If swallowed, get medical help or contact a Poison Control Center right away.

Directions

Shake well, for best result use twice daily or directed by doctor.

Other Information

In rare instances, discoloratin of gray, blonde, bleached or tinted hair may occur.

Inactive Ingredients

Purified water, glycerin (from coconut oil), stearic acid (from coconut oil), pure plant oil complex (soy & jojoba oils), cetylpalmitate (from palm oil), eucalyptus oil, cetearyl alcohol (from palm oil), poly sorbate (from palm oil), glyceryl stearate (from vegetable sources), cetyl alcohol (from palm oil), aminodimethicone (from silica), phenoxyethanol and ethylhexylglycerin (preservative complex from plant source), camphor, menthol, methylparaben, benzoic acid, propylparaben, PEG 150 distearate, vitamin E acetate (DL-alpha-tocopheryl acetate), vitamin A palmitate (Retinyl Palmitate), vitamin H (biotin), polysorbate 80, citric acid.

Question or Comments

Toll free number: 1-855-458-2400, Fax: 1-972-228-2400 or info@albradewynllc.com

Uses

controls symptoms of:

- Seborrheic Dermatitis
- Psoriasis
- Minor & severe dandruff
- relief of sclap & skin itching, irritation & flaking associated with Atopic Dermatiti

Drug Fact

Active Ingredients Purpose

Coal tar solution 1.7% v/v..........................................................................Psoriasis, Atopic & seborrheic

(equivalent to 0.5% coal tar)...................................................................................Dermatitis & Dandruff